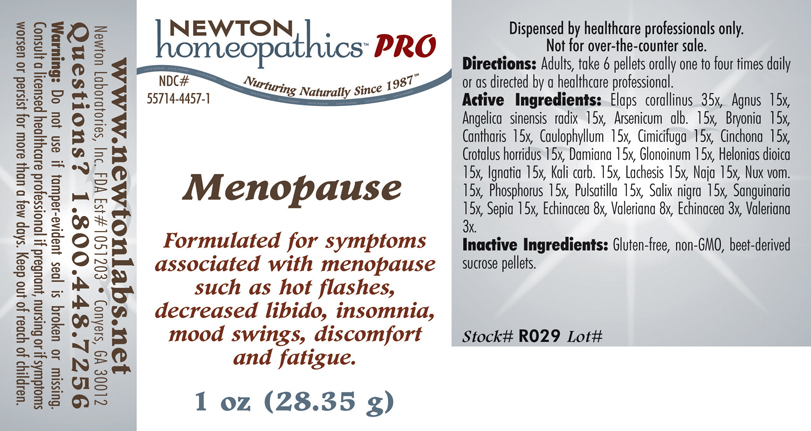 DRUG LABEL: Menopause 
NDC: 55714-4457 | Form: PELLET
Manufacturer: Newton Laboratories, Inc.
Category: homeopathic | Type: HUMAN PRESCRIPTION DRUG LABEL
Date: 20110601

ACTIVE INGREDIENTS: Micrurus Corallinus Venom 35 [hp_X]/1 g; Chaste Tree 15 [hp_X]/1 g; Angelica Sinensis Root 15 [hp_X]/1 g; Arsenic Trioxide 15 [hp_X]/1 g; Bryonia Alba Root 15 [hp_X]/1 g; Lytta Vesicatoria 15 [hp_X]/1 g; Caulophyllum Thalictroides Root 15 [hp_X]/1 g; Black Cohosh 15 [hp_X]/1 g; Cinchona Officinalis Bark 15 [hp_X]/1 g; Crotalus Horridus Horridus Venom 15 [hp_X]/1 g; Turnera Diffusa Leafy Twig 15 [hp_X]/1 g; Nitroglycerin 15 [hp_X]/1 g; Chamaelirium Luteum Root 15 [hp_X]/1 g; Strychnos Ignatii Seed 15 [hp_X]/1 g; Potassium Carbonate 15 [hp_X]/1 g; Lachesis Muta Venom 15 [hp_X]/1 g; Naja Naja Venom 15 [hp_X]/1 g; Strychnos Nux-vomica Seed 15 [hp_X]/1 g; Phosphorus 15 [hp_X]/1 g; Pulsatilla Vulgaris 15 [hp_X]/1 g; Salix Nigra Bark 15 [hp_X]/1 g; Sanguinaria Canadensis Root 15 [hp_X]/1 g; Sepia Officinalis Juice 15 [hp_X]/1 g; Echinacea, Unspecified 8 [hp_X]/1 g; Valerian 8 [hp_X]/1 g
INACTIVE INGREDIENTS: Sucrose

Menopause

INDICATIONS & USAGE SECTION

Menopause Formulated for symptoms associated with menopause such as hot flashes, decreased libido, insomnia, mood swings, discomfort and fatigue.

DOSAGE & ADMINISTRATION SECTION

Directions: Adults, take 6 pellets orally one to four times daily or as directed by a healthcare professional.

ACTIVE INGREDIENT SECTION

Elaps corallinus 35x, Agnus 15x, Angelica sinensis radix 15x, Arsenicum alb. 15x, Bryonia 15x, Cantharis 15x, Caulophyllum 15x, Cimicifuga 15x, Cinchona 15x, Crotalus horridus 15x, Damiana 15x, Glonoinum 15x, Helonias dioica 15x, Ignatia 15x, Kali carb. 15x, Lachesis 15x, Naja 15x, Nux vom.15x, Phosphorus 15x, Pulsatilla 15x, Salix nigra 15x, Sanguinaria 15x, Sepia 15x, Echinacea 8x, Valeriana 8x, Echinacea 3x, Valeriana3x.

PURPOSE SECTION

Formulated for symptoms associated with menopause such as hot flashes, decreased libido, insomnia, mood swings, discomfort and fatigue.

INACTIVE INGREDIENT SECTION

Inactive Ingredients: Gluten-free, non-GMO, beet-derived sucrose pellets.

QUESTIONS? SECTION

www.newtonlabs.net Newton Laboratories, Inc. FDA Est # 1051203 - Conyers, GA 30012
Questions? 1.800.448.7256

WARNINGS SECTION

Warning: Do not use if tamper - evident seal is broken or missing. Consult a licensed healthcare professional if pregnant, nursing or if symptoms worsen or persist for more than a few days. Keep out of reach of children.

PREGNANCY OR BREAST FEEDING SECTION

Consult a licensed healthcare professional if pregnant, nursing or if symptoms worsen or persist for more than a few days.

KEEP OUT OF REACH OF CHILDREN SECTION

Keep out of reach of children.